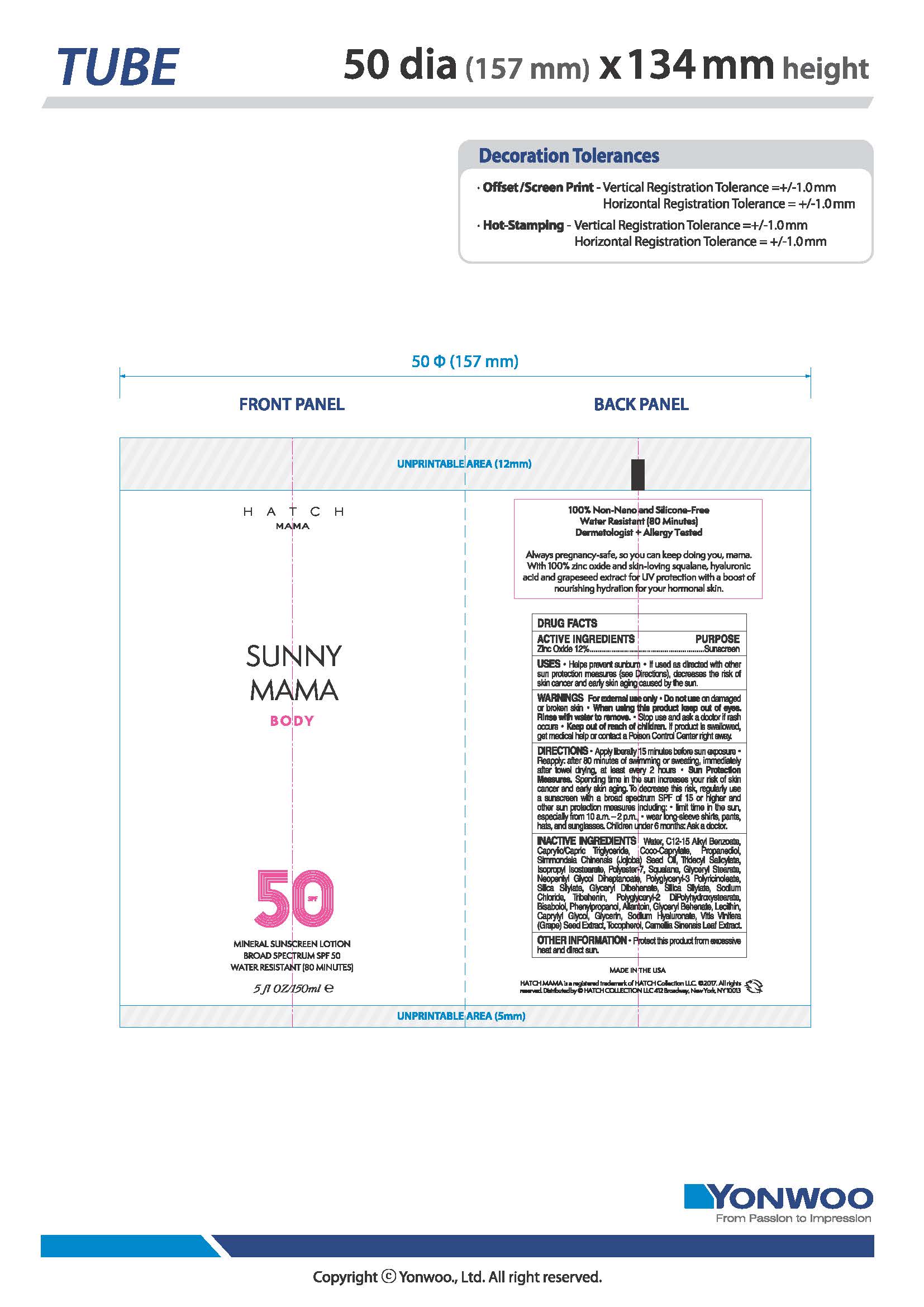 DRUG LABEL: HATCH MAMA SUNNY MAMA Body Mineral Sunscreen Broad Spectrum SPF 50
NDC: 82117-100 | Form: LOTION
Manufacturer: Hatch Collection LLC
Category: otc | Type: HUMAN OTC DRUG LABEL
Date: 20220325

ACTIVE INGREDIENTS: ZINC OXIDE 12 g/100 g
INACTIVE INGREDIENTS: SILICON DIOXIDE; WATER; C12-15 ALCOHOLS; CAPRYLIC/CAPRIC ACID; COCO-CAPRYLATE; PROPANEDIOL; SIMMONDSIA CHINENSIS SEED; TRIDECYL SALICYLATE; ISOPROPYL ISOSTEARATE; POLYESTER-7; SQUALANE; GLYCERYL STEARATE SE; NEOPENTYL GLYCOL; POLYGLYCERYL-3 RICINOLEATE; GLYCERYL DIBEHENATE; SODIUM CHLORIDE; TRIBEHENIN; POLYGLYCERYL-2 DIPOLYHYDROXYSTEARATE; PHENYLPROPANOL; BISABOLOL OXIDE A; ALLANTOIN; LECITHIN, SOYBEAN; CAPRYLYL GLYCOL; GLYCERIN; VITIS VINIFERA SEED; TOCOPHEROL; CAMELLIA SINENSIS SEED

DRUG FACTS

Active Ingredients

Zinc Oxide 12%

Uses

• helps prevent sunburn • if used as directed with other
sun protection measures (see Directions), decreases the
risk of skin cancer and early skin aging caused by the sun

Warnings

For external use only
Do not use on damaged or broken skin
When using this product keep out of eyes. Rinse with water to remove.
Stop use and ask a docor if rash occurs
Keep out of reach of children. If swalled, get medical help or contact a Poison Control Center right away.

Directions

• apply liberally 15 minutes before sun exposure
• reapply:
• after 80 minutes of swimming or sweating
• immediately after towel drying
• at least every 2 hours
• Sun Protection Measures. Spending time in the sun increases your risk
of skin cancer and early skin aging. To decrease this risk, regularly use
a sunscreen with a broad spectrum SPF of 15 or higher and other sun
protection measures including:
• limit time in the sun, especially from 10 a.m. – 2 p.m.
• wear long-sleeve shirts, pants, hats, and sunglasses
• children under 6 months: Ask a doctor

Inactive ingredients

Water, C12-15 Alkyl Benzoate, Caprylic/Capric Triglyceride, Coco-Caprylate, Propanediol, Simmondsia Chinensis (Jojoba) Seed Oil, Tridecyl Salicylate, Isopropyl Isostearate, Polyester-7, Squalane, Glyceryl Stearate, Neopentyl Glycol Diheptanoate, Polyglyceryl-3 Polyricinoleate, Silica Silylate, Glyceryl Dibehenate, Silica, Sodium Chloride, Tribehenin, Polyglyceryl-2 DiPolyhydroxystearate, Bisabolol, Phenylpropanol, Allantoin, Glyceryl Behenate, Lecithin, Caprylyl Glycol, Glycerin, Sodium Hyaluronate, Vitis Vinifera (Grape) Seed Extract, Tocopherol, Camellia Sinensis Leaf Extract.

Other Information

• protect the product in this container from excessive
heat and direct sun